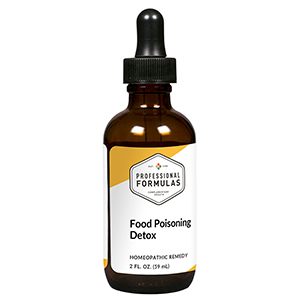 DRUG LABEL: Food Poisoning Detox
NDC: 63083-6023 | Form: LIQUID
Manufacturer: Professional Complementary Health Formulas
Category: homeopathic | Type: HUMAN OTC DRUG LABEL
Date: 20190815

ACTIVE INGREDIENTS: ECHINACEA PURPUREA WHOLE 1 [hp_X]/59 mL; GLYCYRRHIZA GLABRA 1 [hp_X]/59 mL; ACONITUM NAPELLUS WHOLE 3 [hp_X]/59 mL; GOLDENSEAL 5 [hp_X]/59 mL; PODOPHYLLUM 6 [hp_X]/59 mL; ACONITUM LYCOCTONUM WHOLE 6 [hp_X]/59 mL; CITRULLUS COLOCYNTHIS FRUIT PULP 6 [hp_X]/59 mL; ARSENIC TRIOXIDE 6 [hp_X]/59 mL; MERCURIC CHLORIDE 30 [hp_X]/59 mL; MERCURIUS SOLUBILIS 30 [hp_X]/59 mL; CLOSTRIDIUM BOTULINUM 30 [hp_X]/59 mL; HELICOBACTER PYLORI 30 [hp_X]/59 mL; CLOSTRIDIUM DIFFICILE 30 [hp_X]/59 mL; ESCHERICHIA COLI 30 [hp_X]/59 mL; GIBBERELLA FUJIKUROI 30 [hp_X]/59 mL; KLEBSIELLA PNEUMONIAE 30 [hp_X]/59 mL; LISTERIA MONOCYTOGENES 30 [hp_X]/59 mL; SALMONELLA ENTERICA ENTERICA SEROVAR TYPHI 30 [hp_X]/59 mL; STAPHYLOCOCCUS AUREUS 30 [hp_X]/59 mL; STREPTOCOCCUS PYOGENES 30 [hp_X]/59 mL; YERSINIA ENTEROCOLITICA 30 [hp_X]/59 mL
INACTIVE INGREDIENTS: ALCOHOL; WATER

X23

ACTIVE INGREDIENTS

Echinacea purpurea 1X
Glycyrrhiza glabra 1X
Aconitum napellus 3X, 6X, 12X
Hydrastis canadensis 5X
Podophyllum peltatum 6X
Aconitum lycoctonum 6X, 12X
Colocynthis 6X, 12X
Arsenicum album 6X, 12X, 30X
Mercurius corrosivus 30X
Mercurius solubilis 30X
and all the following at 30X, 60X:
Botulinum
Campylobacter pylori bacterium
Clostridium difficile
Escherichia coli
Fusarium
Klebsiella
Listeria
Salmonella typhimurium
Staphylococcus
Streptococcus
Yersinia enterocolitica

QUESTIONS

Professional Formulas

PO Box 2034 Lake Oswego, OR 97035

INDICATIONS

For the temporary relief of cramping, nausea or vomiting, diarrhea, bloating, chills, fatigue, or feelings of discomfort or uneasiness.*

PURPOSE

*Claims based on traditional homeopathic practice, not accepted medical evidence. Not FDA evaluated.

WARNINGS

Consult a doctor if condition worsens or symptoms persist. Keep out of the reach of children. In case of overdose, get medical help or contact a poison control center right away. If pregnant or breastfeeding, ask a healthcare professional before use.

Keep out of the reach of children.

PREGNANCY OR BREAST FEEDING

If pregnant or breastfeeding, ask a healthcare professional before use.

DIRECTIONS

Place drops under tongue 30 minutes before/after meals. Adults and children 12 years and over: Take 10 drops up to 3 times per day. Consult a physician for use in children under 12 years of age.

OTHER INFORMATION

Tamper resistant. If seal is broken, do not use. After opening, close container tightly and store at room temperature away from heat.

INACTIVE INGREDIENTS

20% ethanol, purified water.

LABEL

Est 1985

Professional Formulas

Complementary Health

Food Poisoning Detox

Homeopathic Remedy

2 FL. OZ. (59 mL)